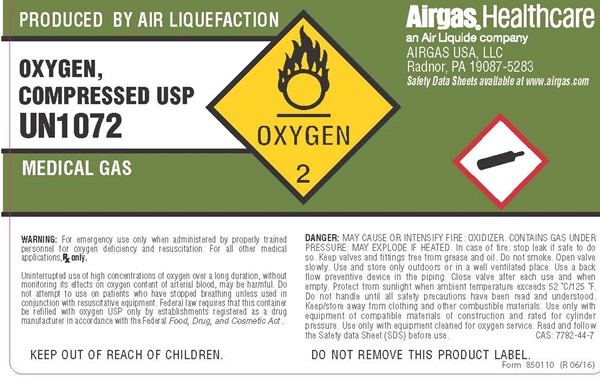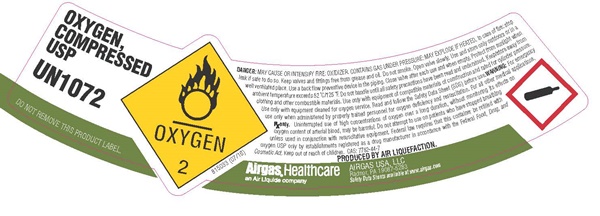 DRUG LABEL: OXYGEN
NDC: 11054-009 | Form: GAS
Manufacturer: Airgas USA, LLC
Category: prescription | Type: HUMAN PRESCRIPTION DRUG LABEL
Date: 20251229

ACTIVE INGREDIENTS: Oxygen 992 mL/1 L

Oxygen, Compressed USP - 009

OXYGEN USP SL

OXYGEN, COMPRESSED USP

UN 1072

DO NOT REMOVE THIS PROODUCT LABEL

OXYGEN 2

815033 (7/16)

DANGER: MAY CAUSE OR INTENSIFY FIRE; OXIDIZER. CONTAINS GAS UNDER PRESSURE. MAY EXPLODE IF HEATED. In case of fire stop leak if safe to do so. Keep valves and fittings free from grease and oil. Do not smoke. Open valve slowly. Use and store only outdoors or in a well ventilated place. Use a back flow preventive device in the piping. Close valve after each use and when empty. Protect from sunlight when ambient temperature exceeds 52° C/125° F. Do not handle until all safety precautions have been read and understood. Keep/store away from clothing and other combustible materials. Use only with equipment of compatible materials of construction and rated for cylinder pressure. Use only with equipment cleaned for oxygen service. Read and follow the Safety Data Sheet (SDS) before use. WARNING: For emergency use only when administered by properly trained personnel for oxygen deficiency and resuscitation. For all other medical applications, Rx only. Uninterrupted use of high concentrations of oxygen over a long duration, without monitoring its effect on oxygen content of arterial blood, may be harmful. Do not attempt to use on patients who have stopped breathing unless used in conjunction with resuscitative equipment. Federal law requires that this container be refilled with oxygen USP only by establishments registered as a drug manufacture in accordance with the Federal Food, Drug, and Cosmetic Act. Keep out of reach of children

CAS: 7782-44-7

PRODUCTED BY AIR LIQUEFACTION.

Airgas,®Healthcare
an Air Liquide company

AIRGAS USA, LLC
Radnor, PA 19087-5283

Safety Data Sheets available at www.airgas.com

OXYGEN USP

PRODUCTED BY AIR LIQUEFACTION.

OXYGEN, COMPRESSED USP

UN 1072

MEDICAL GAS

OXYGEN 2

Airgas,®Healthcare
an Air Liquide company

AIRGAS USA, LLC
Radnor, PA 19087-5283

Safety Data Sheets available at www.airgas.com

WARNING: For emergency use only when administered by properly trained personnel for oxygen deficiency and resuscitation. For all other medical applications, Rx only.

Uninterrupted use of high concentrations of oxygen over a long duration, without monitoring its effect on oxygen content of arterial blood, may be harmful. Do not attempt to use on patients who have stopped breathing unless used in conjunction with resuscitative equipment. Federal law requires that this container be refilled with oxygen USP only by establishments registered as a drug manufacture in accordance with the Federal Food, Drug, and Cosmetic Act.

KEEP OUT OF REACH OF CHILDREN.

DANGER: MAY CAUSE OR INTENSIFY FIRE; OXIDIZER. CONTAINS GAS UNDER PRESSURE. MAY EXPLODE IF HEATED. In case of fire stop leak if safe to do so. Keep valves and fittings free from grease and oil. Do not smoke. Open valve slowly. Use and store only outdoors or in a well ventilated place. Use a back flow preventive device in the piping. Close valve after each use and when empty. Protect from sunlight when ambient temperature exceeds 52° C/125° F. Do not handle until all safety precautions have been read and understood. Keep/store away from clothing and other combustible materials. Use only with equipment of compatible materials of construction and rated for cylinder pressure. Use only with equipment cleaned for oxygen service. Read and follow the Safety Data Sheet (SDS) before use.

CAS: 7782-44-7

DO NOT REMOVE THIS PROODUCT LABEL

Form 850110 (R 06/16)